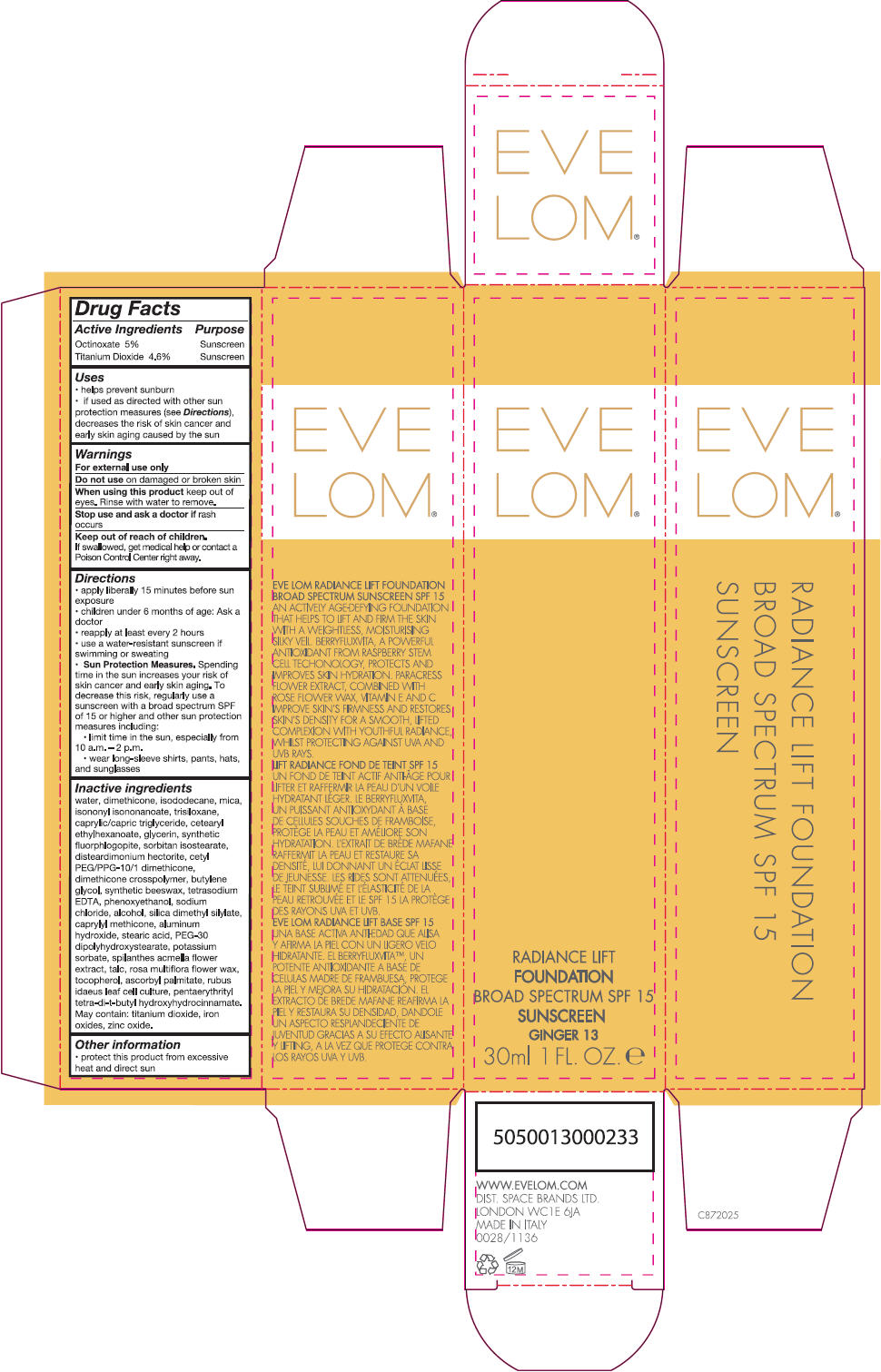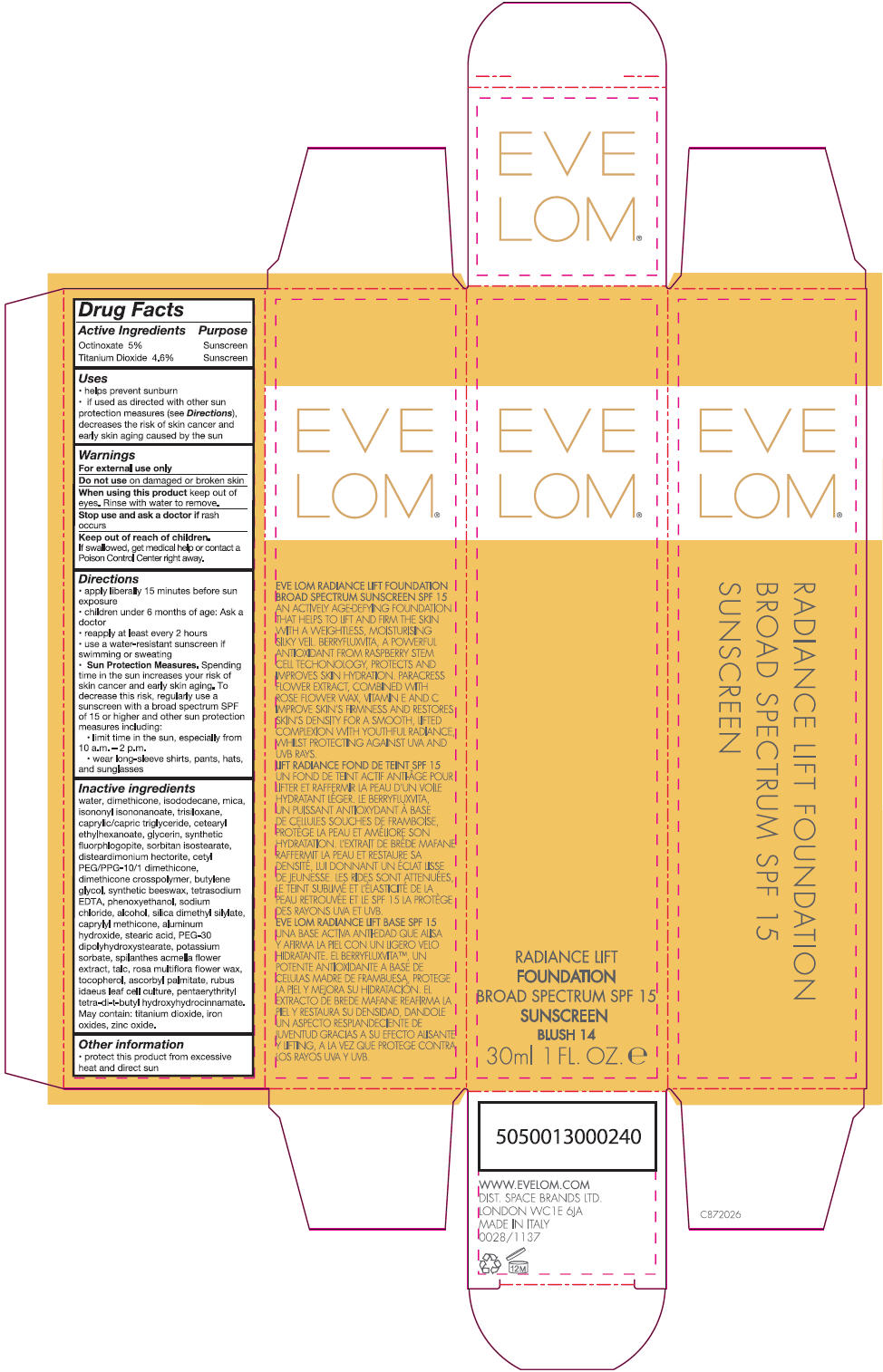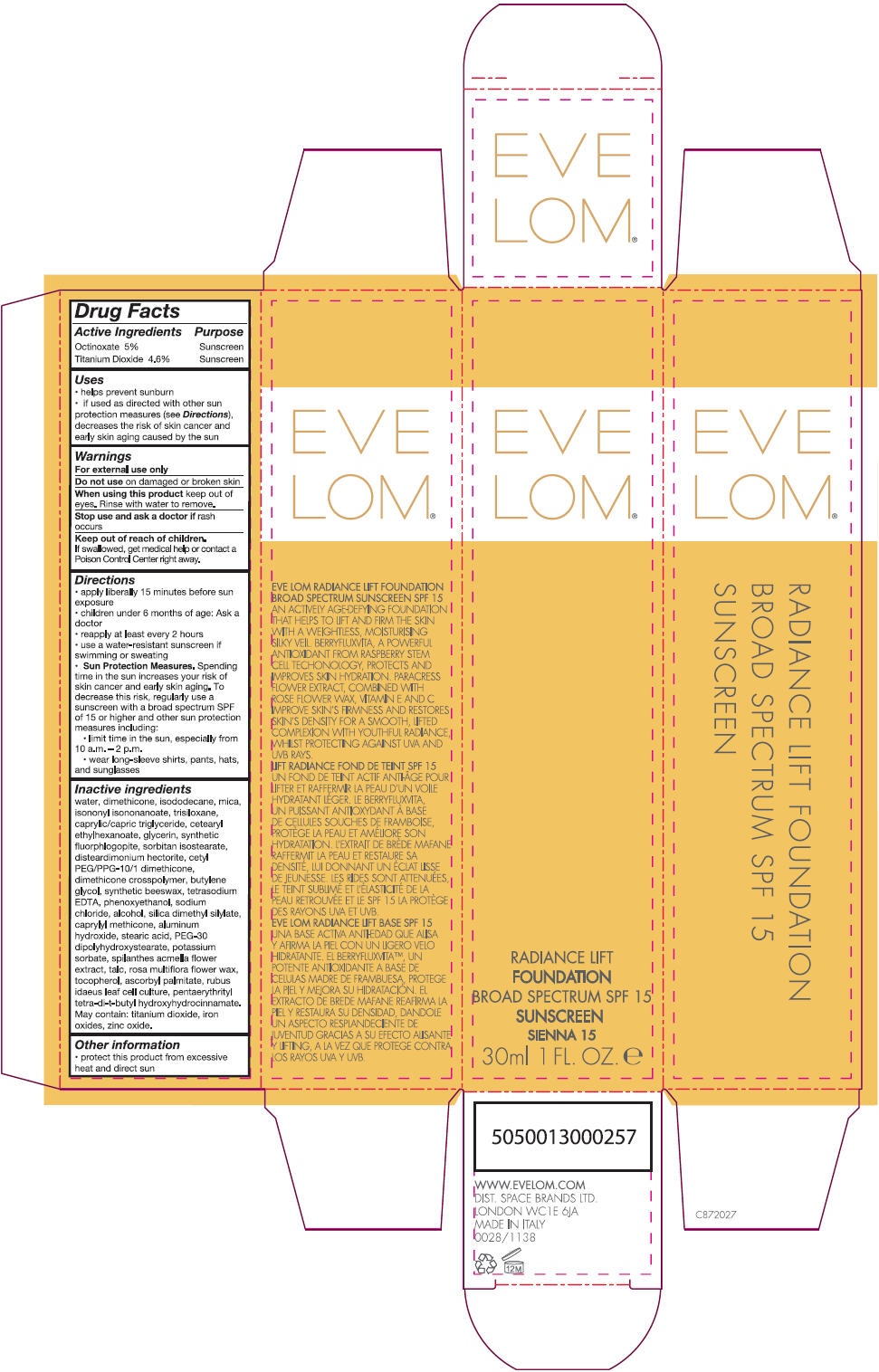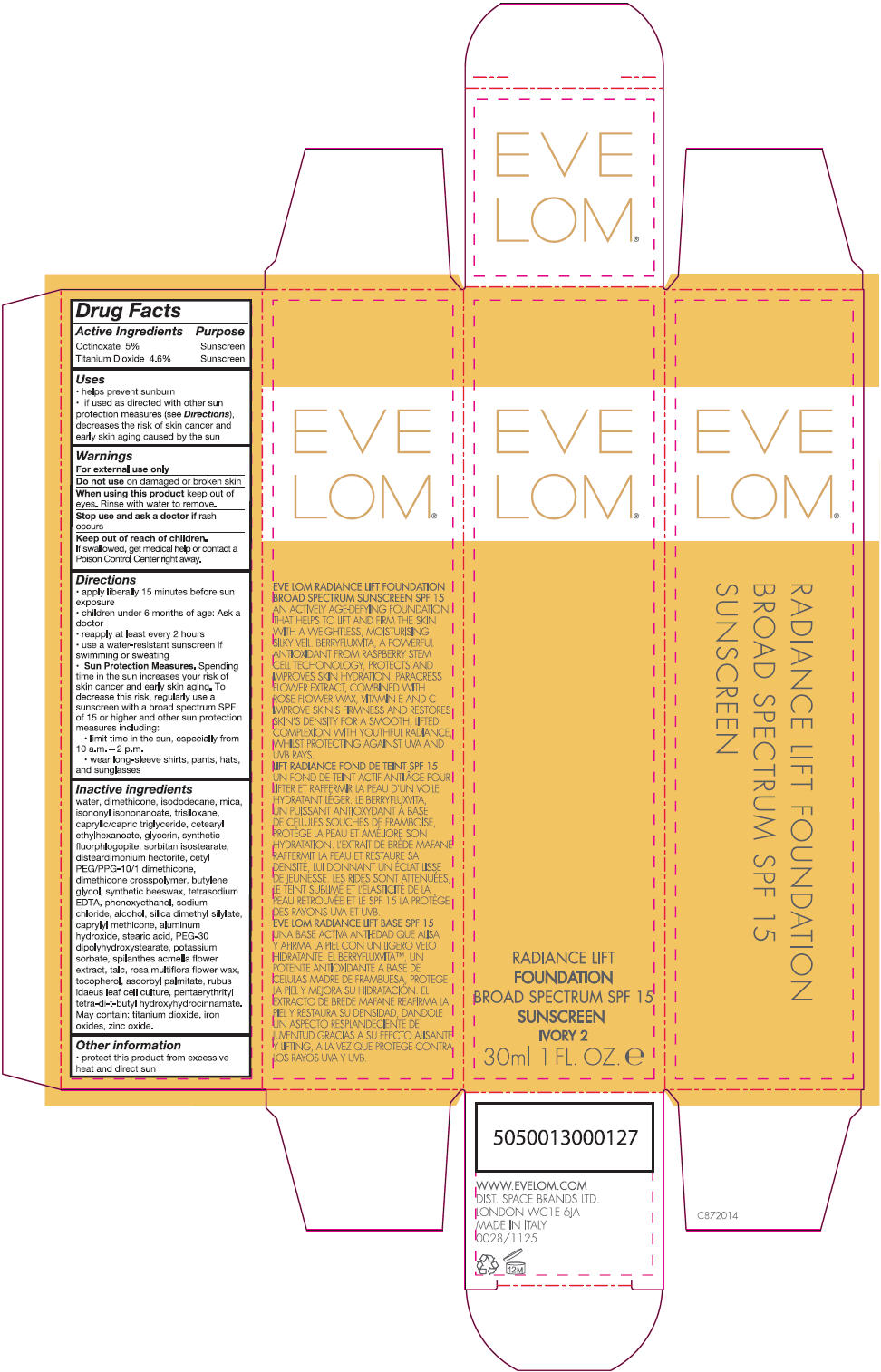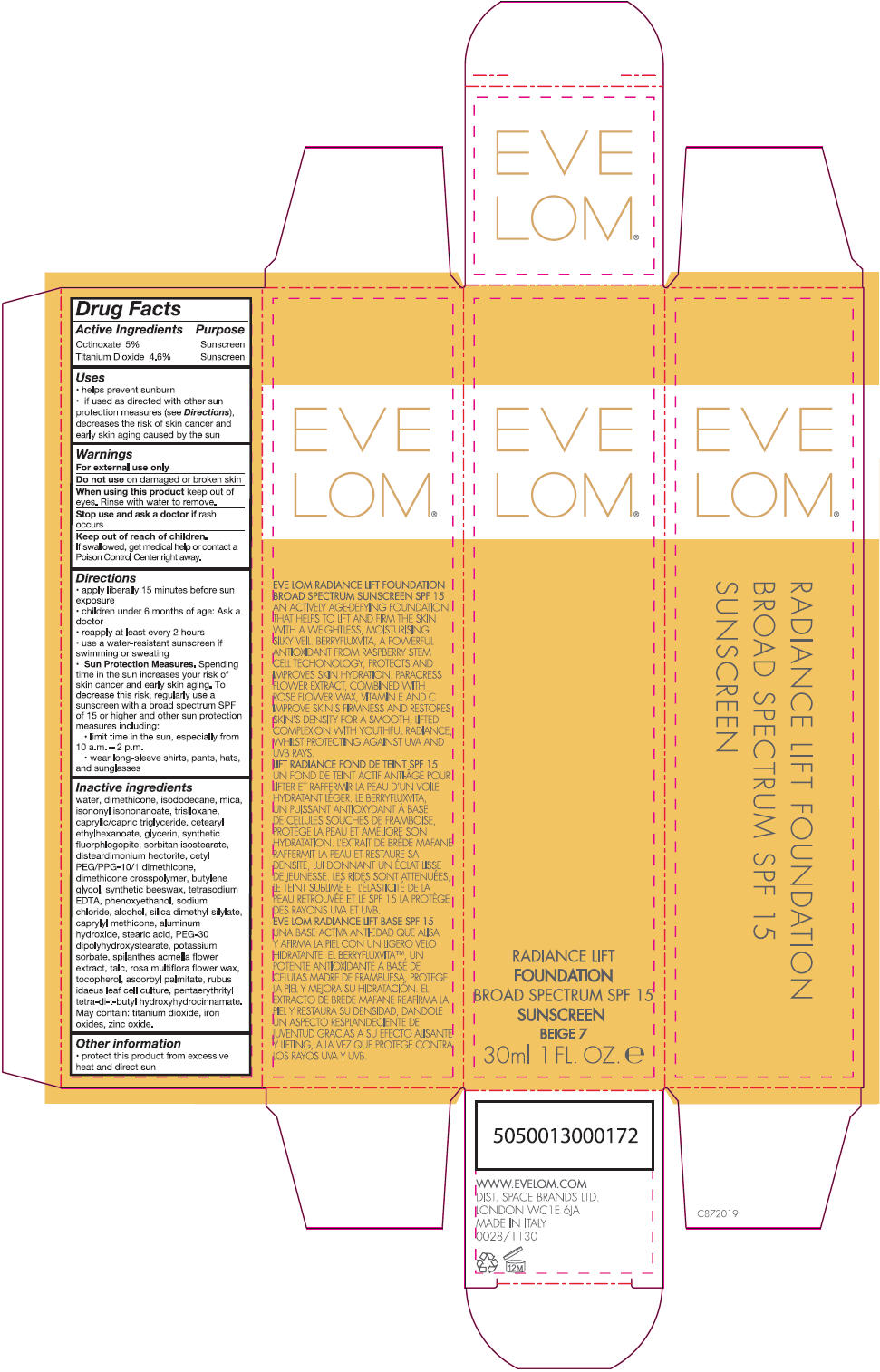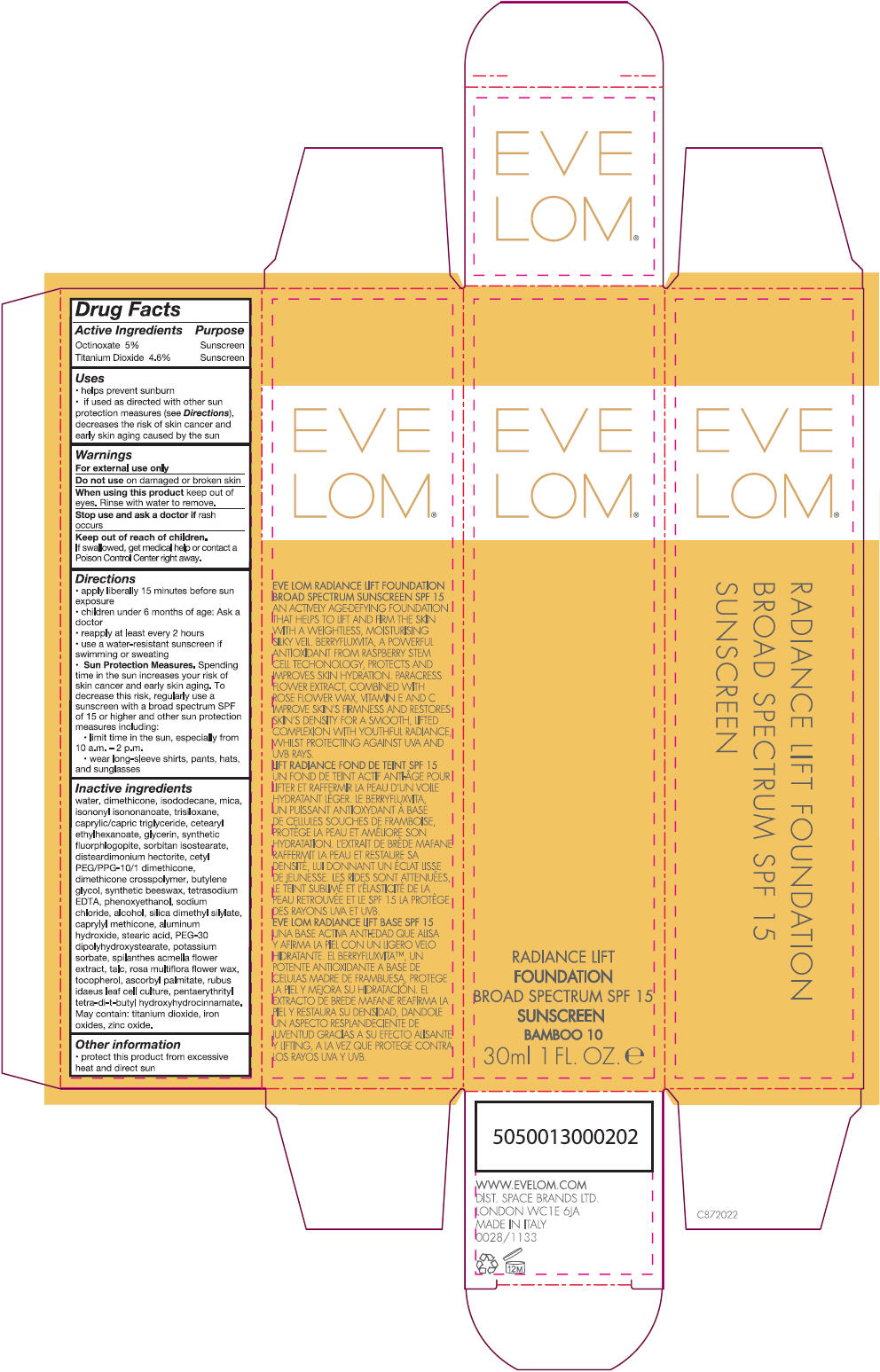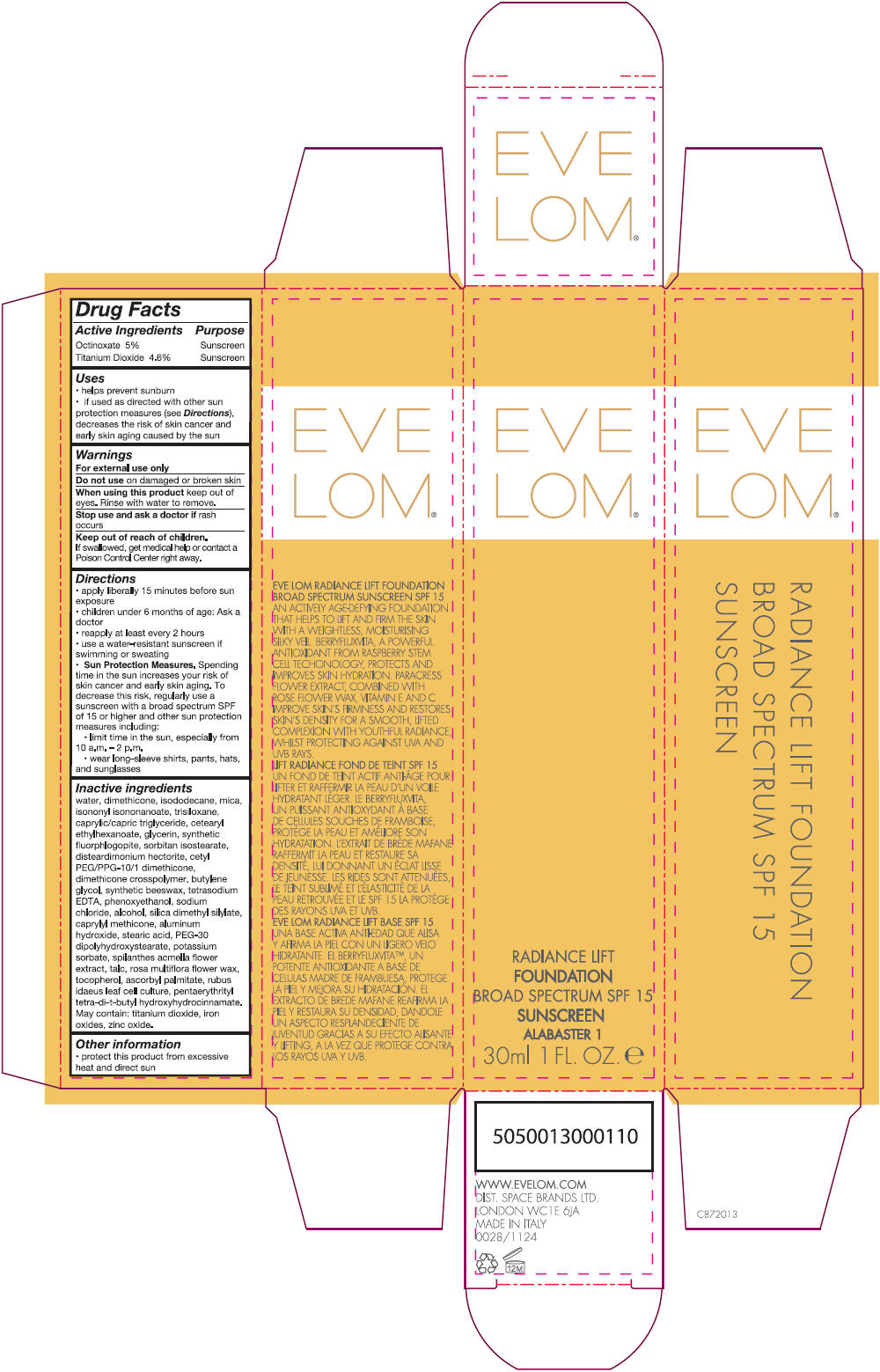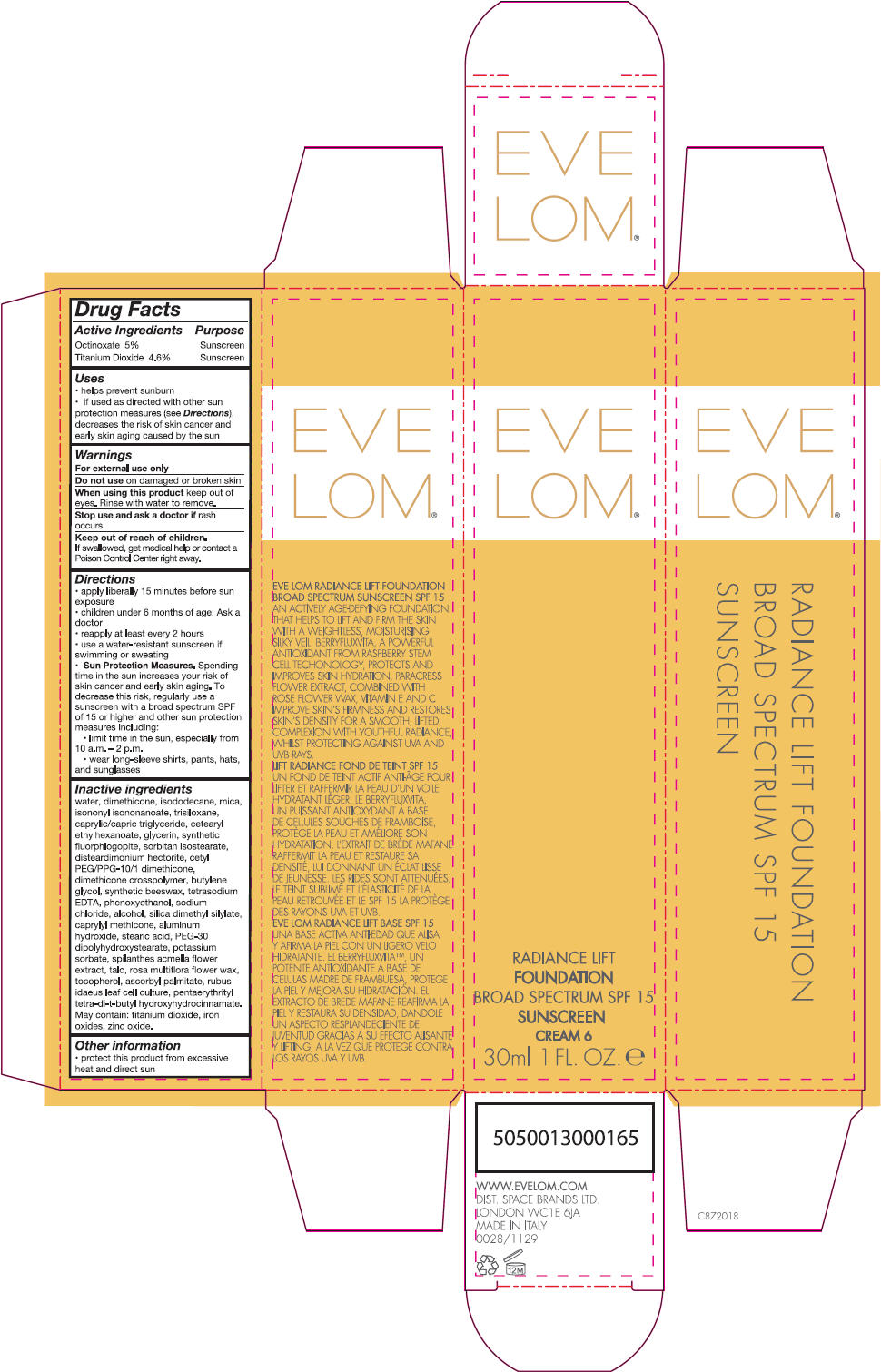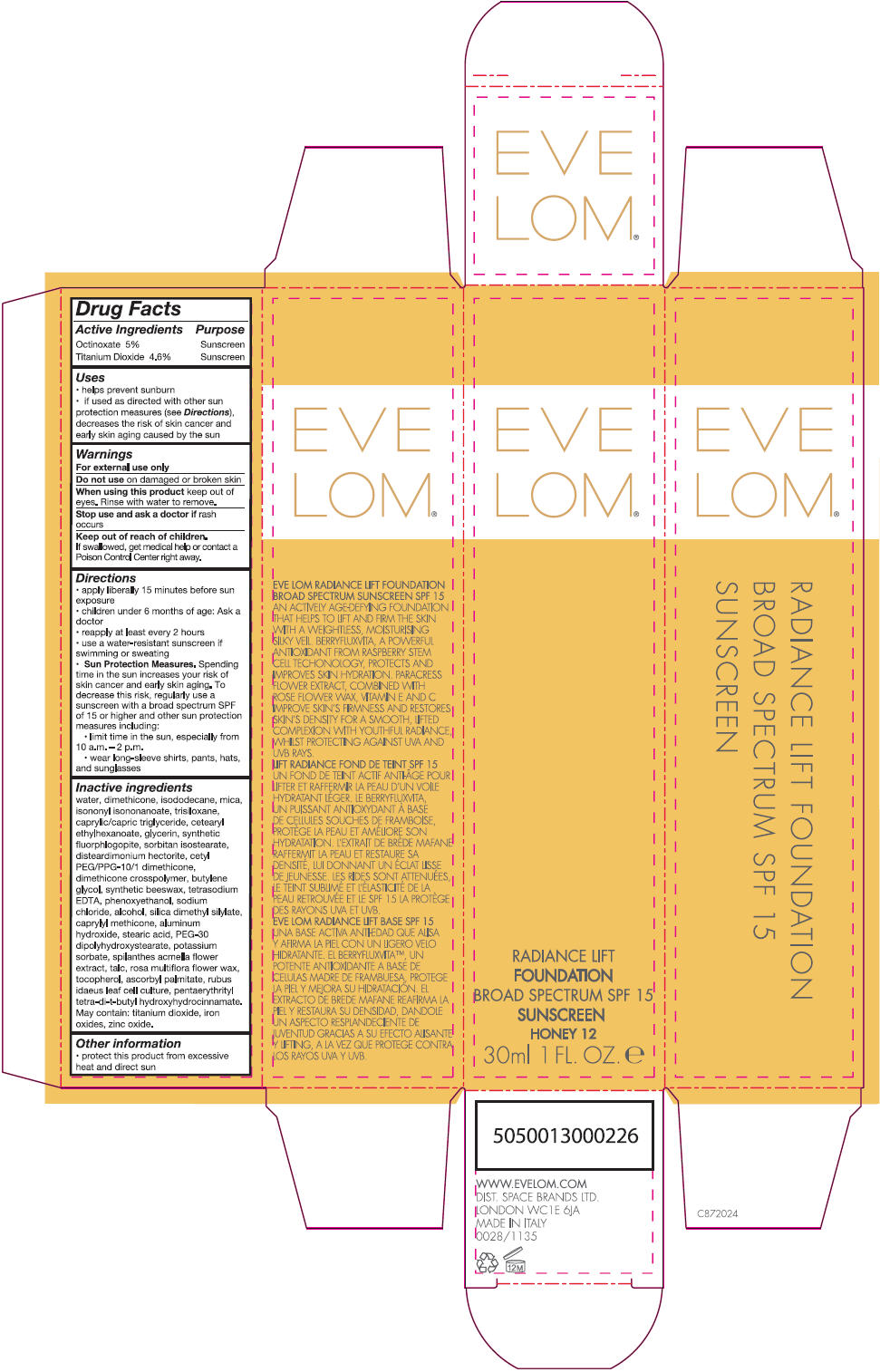 DRUG LABEL: Eve Lom Radiance Lift Foundation SPF 15
NDC: 61601-1136 | Form: CREAM
Manufacturer: Space Brands Limited
Category: otc | Type: HUMAN OTC DRUG LABEL
Date: 20140228

ACTIVE INGREDIENTS: Titanium Dioxide 1.38 g/30 mL; Octinoxate 1.5 g/30 mL
INACTIVE INGREDIENTS: Water; Dimethicone; Isododecane; Mica; Isononyl Isononanoate; Trisiloxane; Ferric Oxide Yellow; Medium-Chain Triglycerides; Cetearyl Ethylhexanoate; Glycerin; Sorbitan Isostearate; Disteardimonium Hectorite; Cetyl PEG/PPG-10/1 Dimethicone (HLB 3); Butylene Glycol; Edetate Sodium; Ferric Oxide Red; Phenoxyethanol; Sodium Chloride; Alcohol; Zinc Oxide; Silica Dimethyl Silylate; Aluminum Hydroxide; Stearic Acid; Caprylyl Trisiloxane; PEG-30 Dipolyhydroxystearate; Ferrosoferric Oxide; Potassium Sorbate; Talc; Acmella Oleracea Flower; Rosa Multiflora Flower Wax; Tocopherol; Ascorbyl Palmitate; Pentaerythritol Tetrakis(3-(3,5-Di-Tert-Butyl-4-Hydroxyphenyl)Propionate)

Eve Lom® Radiance Lift Foundation SPF 15

Drug Facts

ACTIVE INGREDIENT

Active Ingredients | Purpose
Octinoxate 5% | Sunscreen
Titanium Dioxide 4.6% | Sunscreen

Uses

- helps prevent sunburn
- if used as directed with other sun protection measure (see Directions), decreases the risk of skin cancer and early skin aging caused by the sun

Warnings

For external use only

Do not use on damaged or broken skin

When using this product keep out of eyes. Rinse with water to remove.

Stop use and ask a doctor if rash occurs.

Keep out of reach of children. If swallowed, get medical help or contact a Poison Control Center right away.

Directions

- apply liberally 15 minutes before sun exposure
- children under 6 months of age: Ask a doctor
- reapply at least every 2 hours
- use a water-resistant sunscreen if swimming or sweating
- Sun Protection Measures. Spending time in the sun increases your risk of skin cancer and early skin aging. To decrease this risk, regularly use a sunscreen with a broad spectrum SPF of 15 or higher and other sun protection measures including:
  - limit time in the sun, especially from 10 a.m. – 2 p.m.
  - wear long-sleeve shirts, pants, hats, and sunglasses

Inactive ingredients

water, dimethicone, isododecane, mica, isononyl isononanoate, trisiloxane, caprylic/capric triglyceride, cetearyl ethlyhexanoate, glycerin, synthetic fluorphlogopite, sorbitan isostearate, disteardimonium hectorite, cetyl PEG/PPG-10/1 dimethicone, dimethicone crosspolymer, butylene glycol, synthetic beeswax, tetrasodium EDTA, phenoxyethanol, sodium chloride, alcohol, silica dimethyl silylate, caprylyl methicone, aluminum hydroxide, stearic acid, PEG-30 dipolyhydroxystearate, potassium sorbate, spilanthes acmella flower extract, talc, rosa multiflora flower wax, tocopherol, ascorbyl palmitate, rubus idaeus leaf cell culture, pentaerythrityl tetra-di-t-butyl hydroxyhydrocinnamate.

May contain: titanium dioxide, iron oxides, zinc oxide.

Other information

- protect this product from excessive heat and direct sun

PRINCIPAL DISPLAY PANEL - 30 mL Bottle Carton - Ginger 13

EVE
LOM®

RADIANCE LIFT
FOUNDATION
BROAD SPECTRUM SPF 15
SUNSCREEN
GINGER 13
30ml 1 FL. OZ. e

PRINCIPAL DISPLAY PANEL - 30 mL Bottle Carton - Blush 14

EVE
LOM®

RADIANCE LIFT
FOUNDATION
BROAD SPECTRUM SPF 15
SUNSCREEN
BLUSH 14
30ml 1 FL. OZ. e

PRINCIPAL DISPLAY PANEL - 30 mL Bottle Carton - Sienna 15

EVE
LOM®

RADIANCE LIFT
FOUNDATION
BROAD SPECTRUM SPF 15
SUNSCREEN
SIENNA 15
30ml 1 FL. OZ. e

PRINCIPAL DISPLAY PANEL - 30 mL Bottle Carton - Ivory 2

EVE
LOM®

RADIANCE LIFT
FOUNDATION
BROAD SPECTRUM SPF 15
SUNSCREEN
IVORY 2
30ml 1 FL. OZ. e

PRINCIPAL DISPLAY PANEL - 30 mL Bottle Carton - Beige 7

EVE
LOM®

RADIANCE LIFT
FOUNDATION
BROAD SPECTRUM SPF 15
SUNSCREEN
BEIGE 7
30ml 1 FL. OZ. e

PRINCIPAL DISPLAY PANEL - 30 mL Bottle Carton - Bamboo 10

EVE
LOM®

RADIANCE LIFT
FOUNDATION
BROAD SPECTRUM SPF 15
SUNSCREEN
BAMBOO 10
30ml 1 FL. OZ. e

PRINCIPAL DISPLAY PANEL - 30 mL Bottle Carton - Alabaster 1

EVE
LOM®

RADIANCE LIFT
FOUNDATION
BROAD SPECTRUM SPF 15
SUNSCREEN
ALABASTER 1
30ml 1 FL. OZ. e

PRINCIPAL DISPLAY PANEL - 30 mL Bottle Carton - Cream 6

EVE
LOM®

RADIANCE LIFT
FOUNDATION
BROAD SPECTRUM SPF 15
SUNSCREEN
CREAM 6
30ml 1 FL. OZ. e

PRINCIPAL DISPLAY PANEL - 30 mL Bottle Carton - Honey 12

EVE
LOM®

RADIANCE LIFT
FOUNDATION
BROAD SPECTRUM SPF 15
SUNSCREEN
HONEY 12
30ml 1 FL. OZ. e